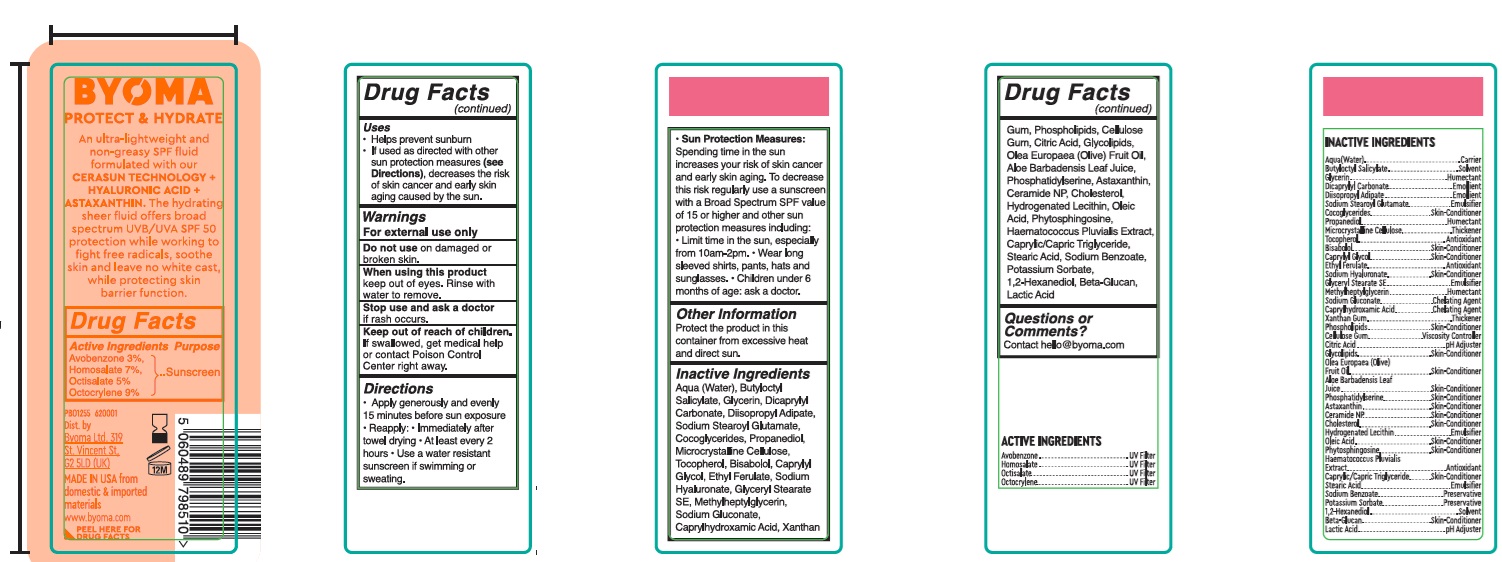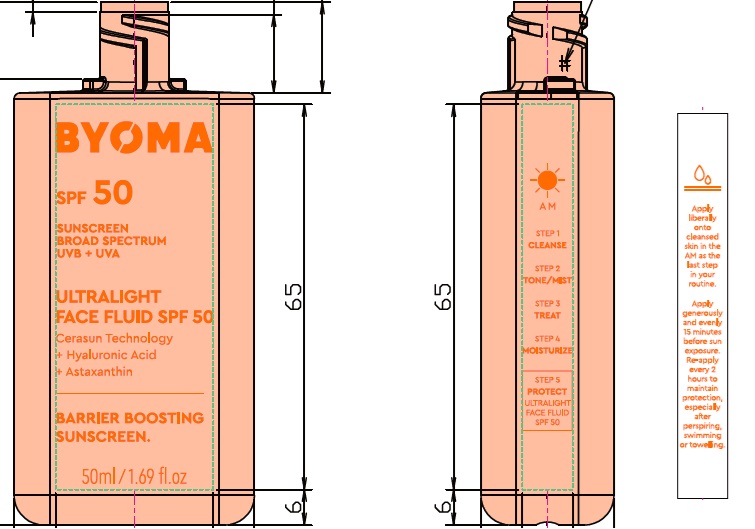 DRUG LABEL: Byoma Ultralight Face Fluid SPF 50
NDC: 84821-003 | Form: LOTION
Manufacturer: BYOMA LIMITED
Category: otc | Type: HUMAN OTC DRUG LABEL
Date: 20241107

ACTIVE INGREDIENTS: AVOBENZONE 30 mg/1 mL; OCTISALATE 50 mg/1 mL; HOMOSALATE 70 mg/1 mL; OCTOCRYLENE 90 mg/1 mL
INACTIVE INGREDIENTS: HAEMATOCOCCUS PLUVIALIS; SODIUM BENZOATE; POTASSIUM SORBATE; ASTAXANTHIN; PHYTOSPHINGOSINE; DICAPRYLYL CARBONATE; DIISOPROPYL ADIPATE; CAPRYLHYDROXAMIC ACID; CERAMIDE NP; SODIUM STEAROYL GLUTAMATE; COCOGLYCERIDES; GLYCERIN; PROPANEDIOL; SODIUM HYALURONATE; XANTHAN GUM; MICROCRYSTALLINE CELLULOSE; CAPRYLYL GLYCOL; ETHYL FERULATE; LEVOMENOL; YEAST .BETA.-D-GLUCAN; SODIUM GLUCONATE; GLYCERYL STEARATE SE; CAPRYLIC/CAPRIC TRIGLYCERIDE; WATER; BUTYLOCTYL SALICYLATE; HYDROGENATED SOYBEAN LECITHIN; STEARIC ACID; OLEIC ACID; OMEGA-3 FATTY ACIDS; LACTIC ACID; CELLULOSE GUM; 1,2-HEXANEDIOL; CITRIC ACID MONOHYDRATE; OLIVE OIL; ALOE VERA LEAF; PHOSPHATIDYLSERINE; TOCOPHEROL; CHOLESTEROL

Byoma Ultralight Face Fluid SPF 50

Active Ingredients

Avobenzone 3%,

Homosalate 7%,

Octisalate 5%

Octocrylene 9%

Purpose

Sunscreen

Uses

- Helps prevent sunburn
- If used as directed wtih other sun protection measures (see Directions), decreases the risk of skin cancer and early skin aging cause by the sun.

Warnings

For external use only

Do not use

on damaged or broken skin.

When using this product

keep out of eyes. Rinse with water to remove.

Stop use and ask a doctor

if rash occurs.

Keep out of reach of children.

If swallowed, get medical help or contact Poison Control Center right away.

Directions

- Apply generously and evenly 15 minutes before sun exposure.
- Reapply: Immediately after towe drying
- At least every 2 hours.
- Use a water resistant sunscreen if swiming or sweating.
- Sun Protection Measures. Spending time in the sun increases your risk of skin cancer and early skin aging. To decrease this risk regularly use a sunscreen with a Broad Spectrum SPF value of 15 or higher and other sun protection measures including:
- Limit time in the sun, especially from 10am-2pm
- Wear long sleeved shirts, pants, hats and sunglasses.
- Children under 6 months of age: ask a doctor.

Other Information

Protect the product in this container from excessive heat and direct sun.

Inactive Ingredients

Aqua (Water), Butyloctyl Salicylate, Glycerin, Dicaprylyl Carbonate, Diisopropyl Adipate, Sodium Stearoyl Glutamate, Cocoglycerides, Propanediol, Microcrystalline Cellulose, Tocopherol, Bisabolol, Caprylyl Glycol, Ethyl Ferulate, Sodium Hyaluronate, Glyceryl Stearate SE, Methylheptylglycerin, Sodium Gluconate, Caprylhydroxamic Acid, Xanthan Gum, Phospholipids, Cellulose Gum, Citric Acid, Glycolipids, Olea Europaea (Olive) Fruit Oil, Aloe Barbadensis Leaf Juice, Phosphatidylserine, Astaxanthin, Ceramide NP, Cholesterol, Hydrogenated Lecithin, Oleic Acid, Phytosphingosine, Haematococcus Pluvialis Extract, Caprylic/Capric Triglyceride, Stearic Acid, Sodium Benzoate, Potassium Sorbate, 1,2-Hexanediol, Beta-Glucan, Lactic Acid

Questions or Comments?

contact hello@byoma.com